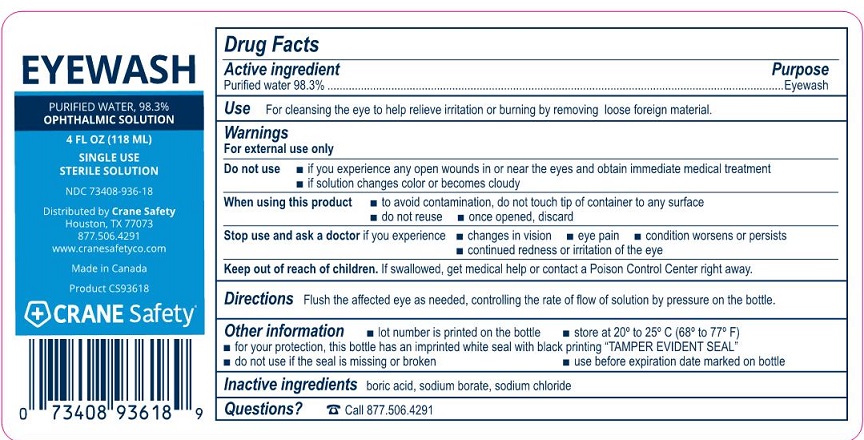 DRUG LABEL: Crane Safety Eye Wash
NDC: 73408-936 | Form: SOLUTION
Manufacturer: Crane Safety LLC
Category: otc | Type: HUMAN OTC DRUG LABEL
Date: 20241108

ACTIVE INGREDIENTS: WATER 0.983 mg/1 mL
INACTIVE INGREDIENTS: SODIUM BORATE; SODIUM CHLORIDE; BORIC ACID

Crane Safety Eye Wash

Active ingredient

Purified water 98.3%

Purpose

Eye wash

Uses

For cleansing the eye to remove loose foreign material and to also releive irritation and burning.

Warnings

For external use only

Do not use

- if you experience any open wounds in or near the eyes and get medical help right away
- if solution changes color or becomes cloudy

When using this product

- to avoid contamination, do not touch tip of container to any surface
- do not reuse
- once opened, discard

Stop use and ask a doctor if

you experience

- eye pain
- changes in vision
- continued redness or irritation of the eye
- condition worsens or persists

Keep out of reach of children.

Directions

Flush the affected eye as needed, controlling the rate of flow of solution by pressure on the bottle.

Other information

- for your protection, this bottle has an imprinted white seal with black printing “TAMPER EVIDENT SEAL”
- do not use if this seal is missing or broken
- use before expiration date marked on bottle
- lot number is printed on the bottle
- store at 20º to 25º C [68º to 77º F]

Inactive ingredients

boric acid, sodium borate, sodium chloride

Questions or comments?

877.506.4291

Crane Safety Eye Wash Label

Eyewash

Purified Water, 98.3%

Ophthalmic Solution

4 Fl oz (118 mL)

Single Use Sterile Solution

NDC 73408-936-18

Distributed by Crane Safety

Houston TX 77073

877.506.4291

www.cranesafetyco.com

Made in Canada

Product CS93618

CRANE Safety®